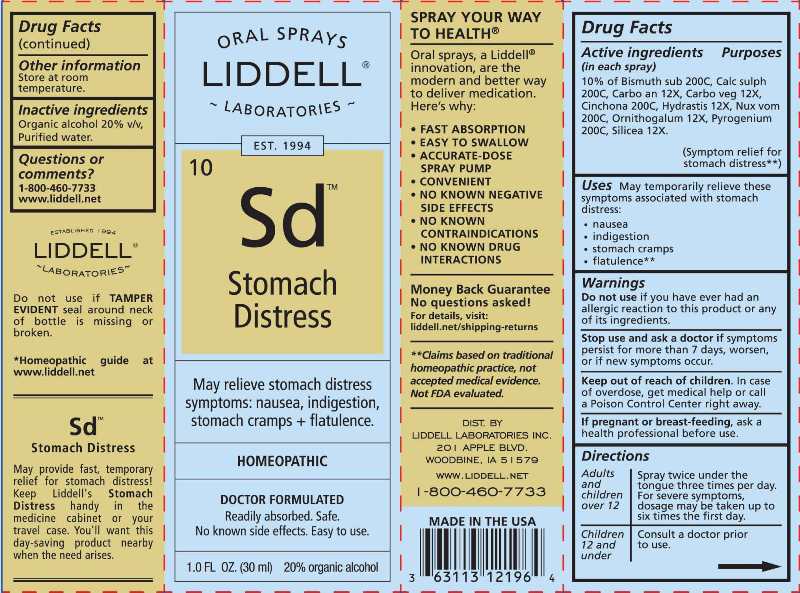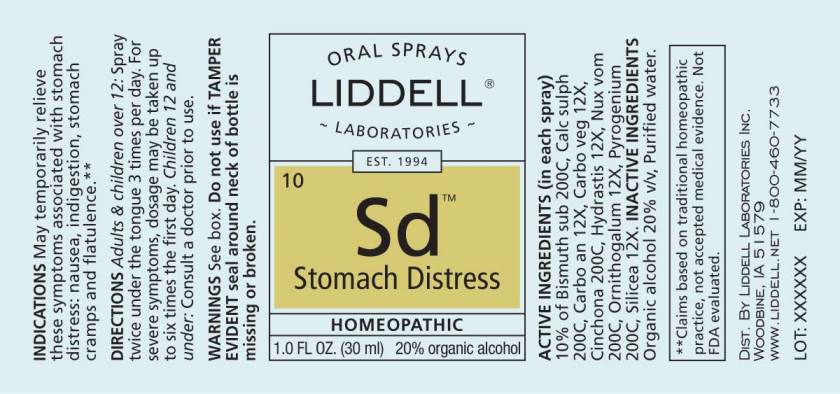 DRUG LABEL: Stomach Distress
NDC: 50845-0253 | Form: SPRAY
Manufacturer: Liddell Laboratories, Inc.
Category: homeopathic | Type: HUMAN OTC DRUG LABEL
Date: 20230911

ACTIVE INGREDIENTS: BISMUTH SUBNITRATE 200 [hp_C]/1 mL; CALCIUM SULFATE ANHYDROUS 200 [hp_C]/1 mL; CARBO ANIMALIS 12 [hp_X]/1 mL; ACTIVATED CHARCOAL 12 [hp_X]/1 mL; CINCHONA OFFICINALIS BARK 200 [hp_C]/1 mL; GOLDENSEAL 12 [hp_X]/1 mL; STRYCHNOS NUX-VOMICA SEED 200 [hp_C]/1 mL; ORNITHOGALUM UMBELLATUM WHOLE 12 [hp_X]/1 mL; RANCID BEEF 200 [hp_C]/1 mL; SILICON DIOXIDE 12 [hp_X]/1 mL
INACTIVE INGREDIENTS: WATER; ALCOHOL

DRUG FACTS:

ACTIVE INGREDIENTS:

(in each spray) 10% of Bismuthum Subnitricum 200C, Calcarea Sulphurica 200C, Carbo Animalis 12X, Carbo Vegetabilis 12X, Cinchona Officinalis 200C, Hydrastis Canadensis 12X, Nux Vomica 200C, Ornithogalum Umbellatum 12X, Pyrogenium 200C, Silicea 12X.

USES:

May temporarily relieve these symptoms associated with stomach distress:

• nausea

• indigestion

• stomach cramps

• flatulence**

**Claims based on traditional homeopathic practice, not accepted medical evidence. Not FDA evaluated.

WARNINGS:

Do not use if you have ever had an allergic reaction to this product or any of its ingredients.

Stop use and ask a doctor if symptoms persist for more than 7 days, worsen, or if new symptoms occur.

Keep out of reach of children. In case of overdose, get medical help or call a Poison Control Center right away.

If pregnant or breast feeding, ask a health professional before use.

Store at room temperature.

Do not use if TAMPER EVIDENT seal around neck of bottle is missing or broken.

Keep out of reach of children. In case of overdose, get medical help or call a Poison Control Center right away.

DIRECTIONS:

Adults and children over 12: Spray twice under the tongue three times per day. For severe symptoms, dosage may be taken up to six times the first day.

Children 12 and under: Consult a doctor prior to use.

INDICATIONS:

May temporarily relieve these symptoms associated with stomach distress:

• nausea

• indigestion

• stomach cramps

• flatulence**

**Claims based on traditional homeopathic practice, not accepted medical evidence. Not FDA evaluated.

INACTIVE INGREDIENTS:

Organic alcohol 20% v/v, Purified water.

QUESTIONS:

DIST. BY

LIDDELL LABORATORIES INC.

201 APPLE BLVD.

WOODBINE, IA 51579

WWW.LIDDELL.NET

1-800-460-7733

PACKAGE LABEL DISPLAY:

ORAL SPRAYS
LIDDELL LABORATORIES

EST. 1994

^10 Sd

Stomach

Distress

May relieve stomach distress

symptoms: nausea, indigestion,

stomach cramps + flatulence.

HOMEOPATHIC

DOCTOR FORMULATED

Readily absorbed. Safe.

No known side effects. Easy to use.

1.0 FL OZ (30 ml)